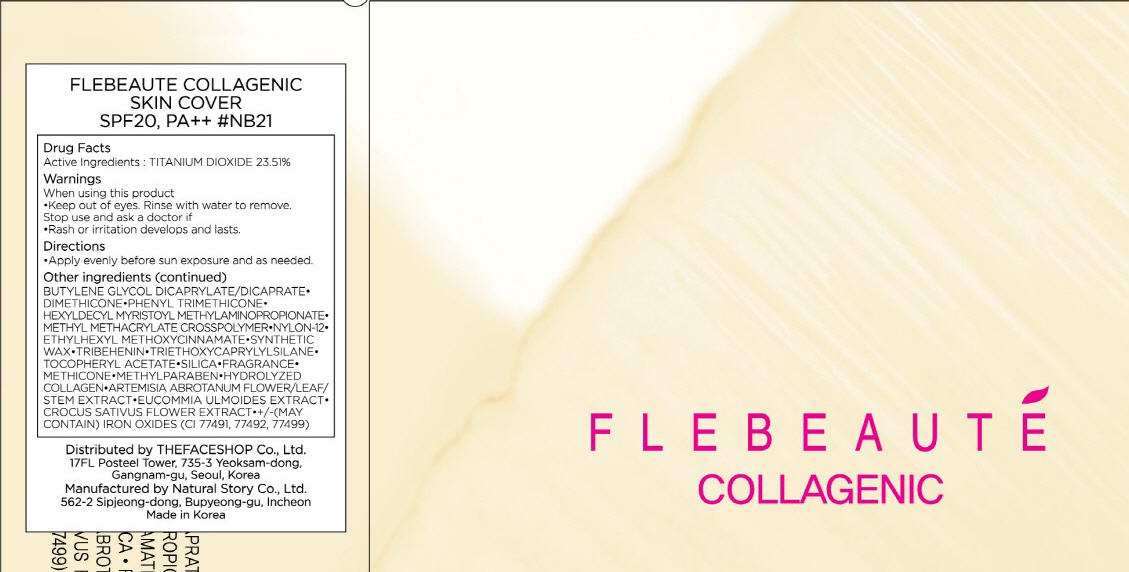 DRUG LABEL: FLEBEAUTE COLLAGENIC SKIN COVER
NDC: 51523-007 | Form: CREAM
Manufacturer: THEFACESHOP CO., LTD.
Category: otc | Type: HUMAN OTC DRUG LABEL
Date: 20100714

ACTIVE INGREDIENTS: TITANIUM DIOXIDE 2.35 g/10 g

Drug Facts

Active Ingredient: TITANIUM DIOXIDE

Inactive Ingredients:
BUTYLENE GLYCOL DICAPRYLATE/DICAPRATE, DIMETHICONE, PHENYL TRIMETHICONE, HEXYLDECYL MYRISTOYL METHYLAMINOPROPIONATE, METHYL METHACRYLATE CROSSPOLYMER, NYLON-12, ETHYLHEXYL METHOXYCINNAMATE, SYNTHETIC WAX, TRIBEHENIN, TRIETHOXYCAPRYLYLSILANE, TOCOPHERYL ACETATE, SILICA, FRAGRANCE, METHICONE, METHYLPARABEN, HYDROLYZED COLLAGEN, ARTEMISIA ABROTANUM FLOWER/LEAF/STEM EXTRACT, EUCOMMIA ULMOIDES EXTRACT, CROCUS SATIVUS FLOWER EXTRACT,
(MAY CONTAIN) IRON OXIDES(CI 77491, 77492, 77499)

Warnings:
When using this product
Keep out of eyes. Rinse with water to remove.
Stop use and ask a doctor if
Rash or irritation develops and lasts.
Directions:
Apply evenly before sun exposure and as needed.